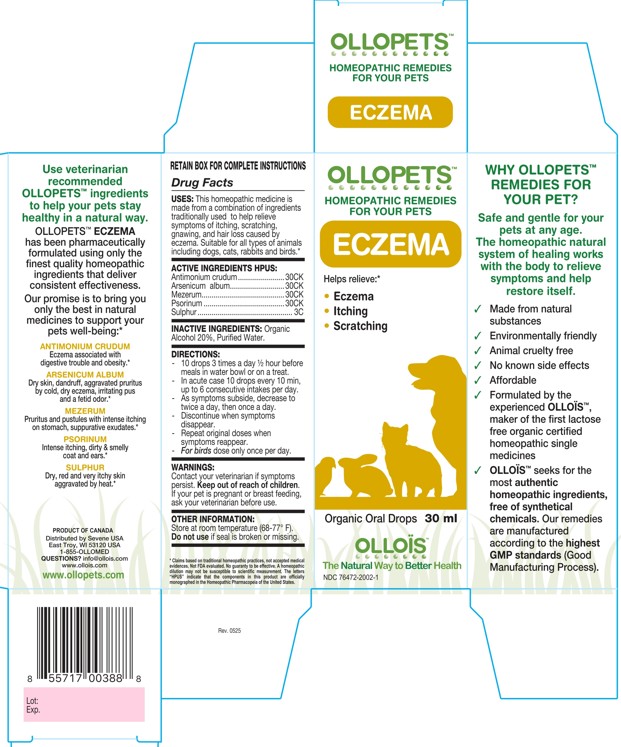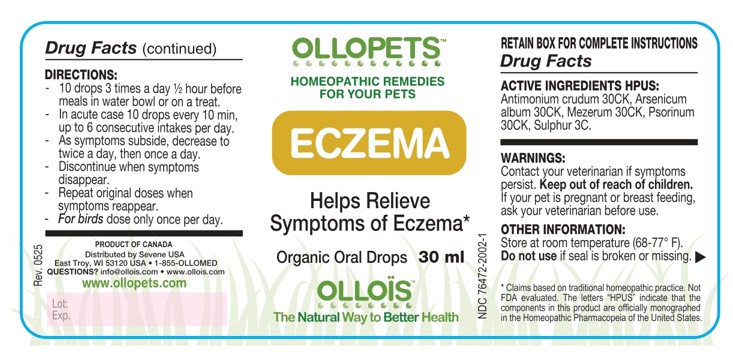 DRUG LABEL: OLLOPETS ECZEMA
NDC: 76472-2002 | Form: SOLUTION
Manufacturer: SEVENE USA
Category: homeopathic | Type: OTC ANIMAL DRUG LABEL
Date: 20260217

ACTIVE INGREDIENTS: ANTIMONY TRISULFIDE 30 [hp_C]/100 mL; ARSENIC TRIOXIDE 30 [hp_C]/100 mL; DAPHNE MEZEREUM BARK 30 [hp_C]/100 mL; SCABIES LESION LYSATE (HUMAN) 30 [hp_C]/100 mL; SULFUR 3 [hp_C]/100 mL
INACTIVE INGREDIENTS: ALCOHOL; WATER

SEVENE USA - OLLOPETS - ECZEMA

ACTIVE INGREDIENT HPUS

Antimonium crudum.......................30CK
Arsenicum album...........................30CK
Mezerum.........................................30CK
Psorinum ........................................30CK
Sulphur ............................................... 3C